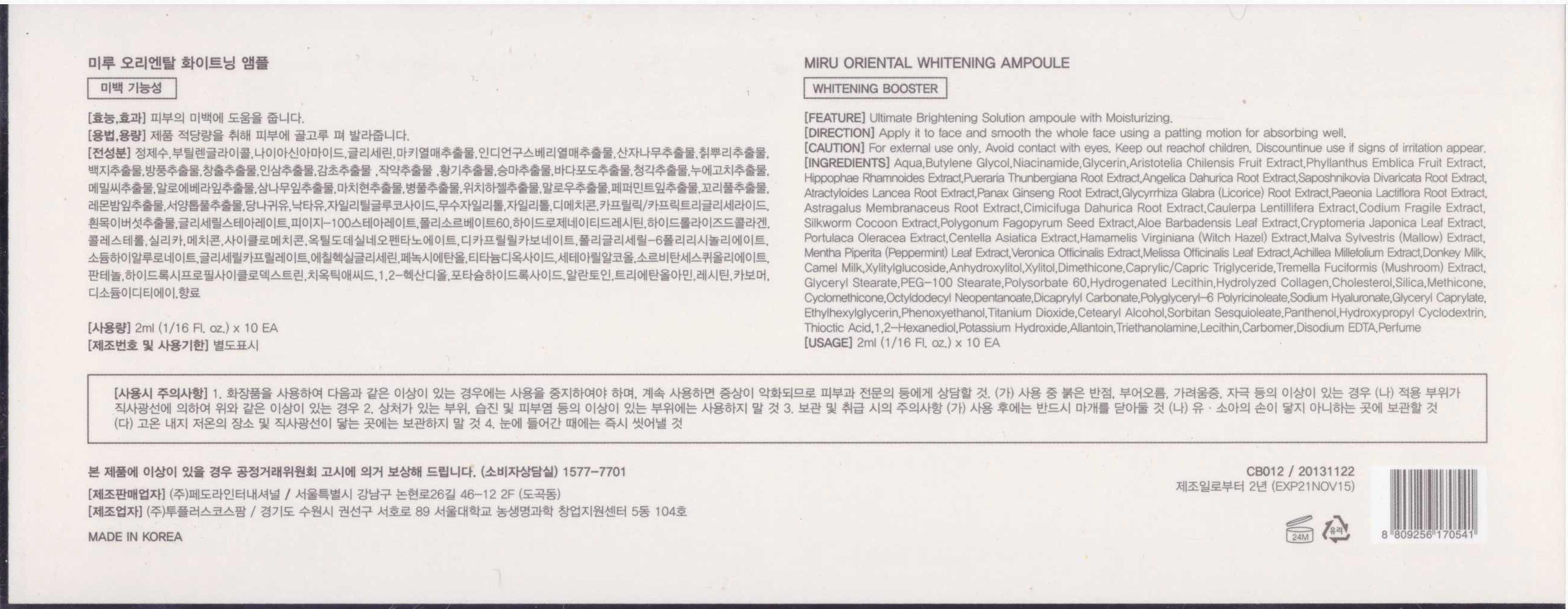 DRUG LABEL: MIRU Oriental Whitening Ampoule
NDC: 62620-2001 | Form: LIQUID
Manufacturer: Fedora International Co., Ltd.
Category: otc | Type: HUMAN OTC DRUG LABEL
Date: 20140306

ACTIVE INGREDIENTS: GLYCERIN 0.0224 g/1 mL
INACTIVE INGREDIENTS: WATER; HYALURONATE SODIUM; BUTYLENE GLYCOL; EDETATE DISODIUM

Drug Facts

ACTIVE INGREDIENT

glycerin

INACTIVE INGREDIENT

Aqua, Butylene Glycol, Niacinamide, Glycerin, Aristotelia Chilensis Fruit Extract, Phyllanthus Emblica Fruit Extract, Hippophae Rhamnoides Extract, Pueraria Thunbergiana Root Extract, Angelica Dahurica Root Extract, Saposhnikovia Divaricata Root Extract, Atractyloides Lancea Root Extract, Panax Ginseng Root Extract, Glycyrrhiza Glabra (Licorice) Root Extract, Paeonia Lactiflora Root Extract, Astragalus Membranaceus Root Extract, Cimicifuga Dahurica Root Extract, Caulerpa Lentillifera Extract, Codium Fragile Extract,, Silkworm Cocoon Extract, Polygonum Fagopyrum Seed Extract, Aloe Barbadensis Leaf Extract, Cryptomeria Japonica Leaf Extract, Portulaca Oleracea Extract, Centella Asiatica Extract, Hamamelis Virginiana (Witch Hazel) Extract, Malva Sylvestris (Mallow) Extract, Mentha Piperita (Peppermint) Leaf Extract, Veronica Officinalis Extract, Melissa Officinalis Leaf Extract, Achillea Millefolium Extract, Donkey Milk, Camel Milk, Xylitylglucoside, Anhydroxylitol, Xylitol, Dimethicone, Caprylic/Capric Triglyceride, Tremella Fuciformis (Mushroom) Extract, Glyceryl Stearate, PEG-100 Stearate, Hydrogenated Lecithin, Hydrolyzed Collagen, Cholesterol, Silica, Methicone, Cyclomethicone, Octyldodecyl Neopentanoate, Dicaprylyl Carbonate, Polyglyceryl-6 polyricinoleate, Sodium Hyaluronate, Glyceryl Caprylate, Ethylhexylglycerin, Phenoxyethanol, Titanium Dioxide, Cetearyl Alcohol , Sorbitan Sesquioleate, Panthenol, Hydroxypropyl Cyclodextrin, Thioctic Acid, 1,2-Hexanediol, Potassium Hydroxide, Allantoin, Triethanolamine, Lecithin, Carbomer, Disodium EDTA, Perfume

PURPOSE

ultimate brightening solution ampoule with moisturizing

keep out of reach of the children

INDICATIONS AND USAGE

apply it to face and smooth the whole face using a patting motion for absorbing well

WARNINGS

avoid contact with eyes
discontinue use if signs of irritation appear

DOSAGE AND ADMINISTRATION

for external use only